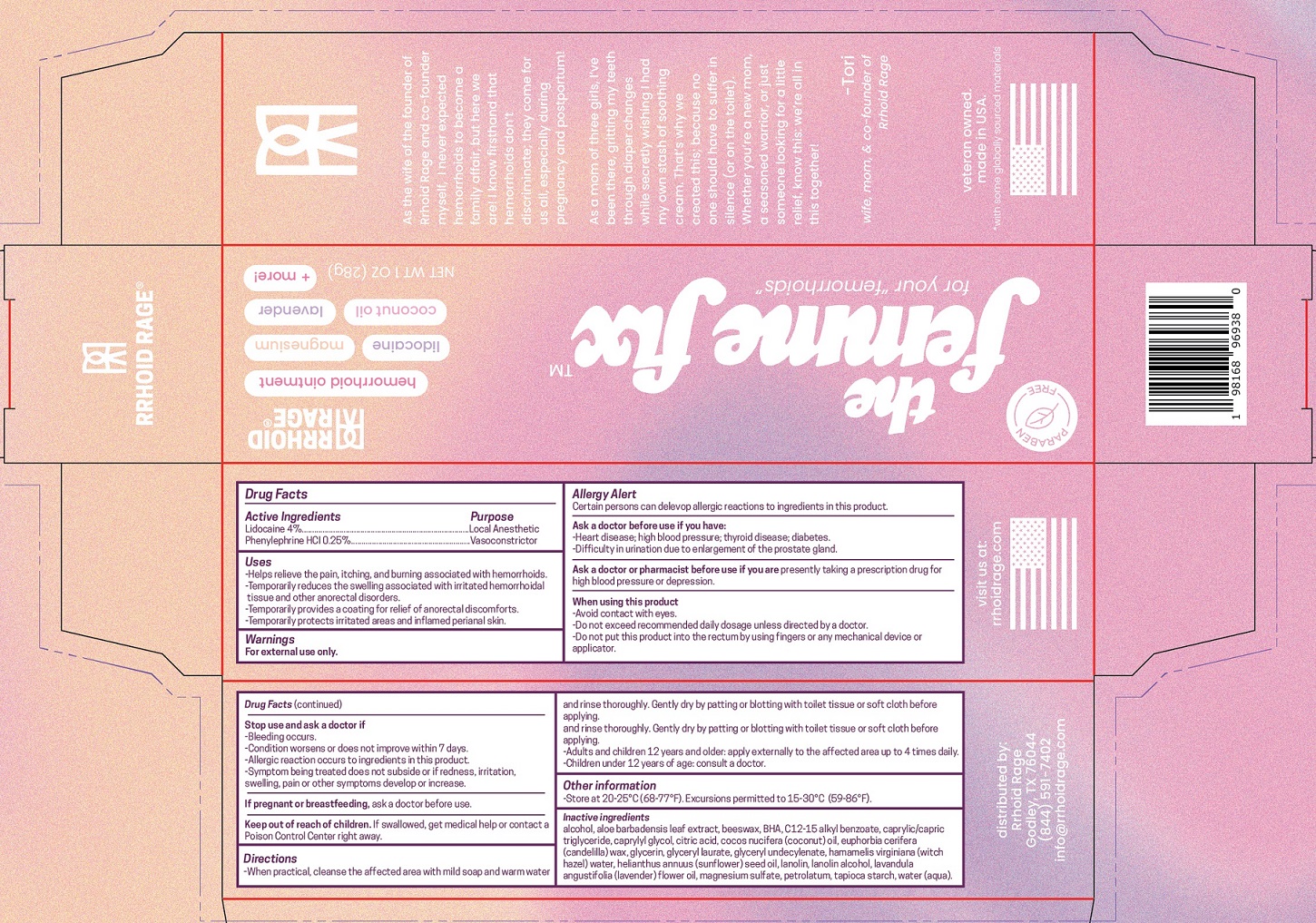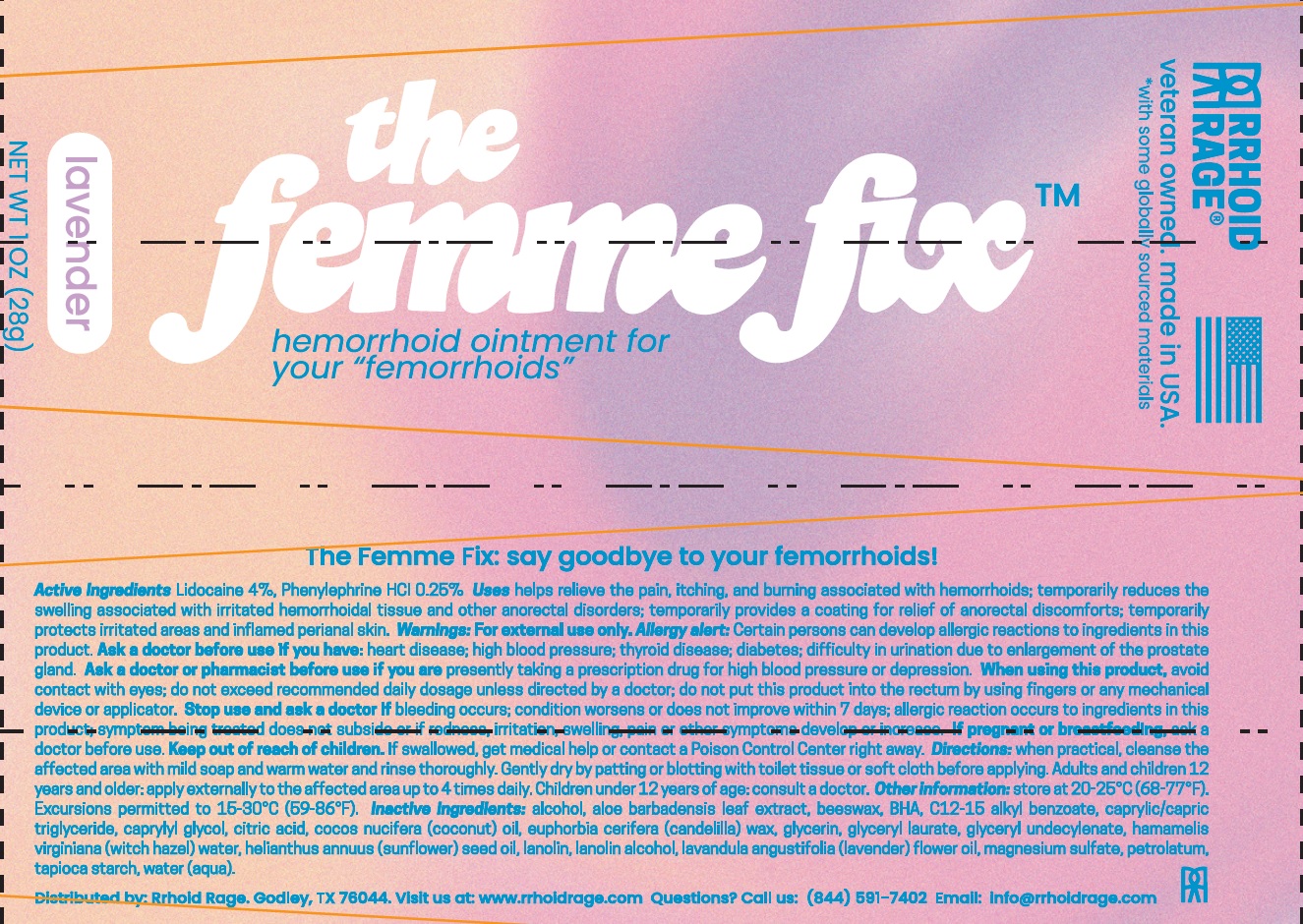 DRUG LABEL: The Femme Fix Hemorrhoid Treatment
NDC: 82433-946 | Form: OINTMENT
Manufacturer: POPPY COLLECTIVE LLC
Category: otc | Type: HUMAN OTC DRUG LABEL
Date: 20250527

ACTIVE INGREDIENTS: LIDOCAINE 40 mg/1 g; PHENYLEPHRINE HYDROCHLORIDE 2.5 mg/1 g
INACTIVE INGREDIENTS: ALCOHOL; ALOE VERA LEAF; YELLOW WAX; BUTYLATED HYDROXYANISOLE; ALKYL (C12-15) BENZOATE; MEDIUM-CHAIN TRIGLYCERIDES; CAPRYLYL GLYCOL; CITRIC ACID MONOHYDRATE; COCONUT OIL; CANDELILLA WAX; GLYCERIN; GLYCERYL LAURATE; HAMAMELIS VIRGINIANA TOP WATER; SUNFLOWER OIL; LANOLIN; LANOLIN ALCOHOLS; MAGNESIUM SULFATE, UNSPECIFIED FORM; PETROLATUM; STARCH, TAPIOCA; WATER

The Femme Fix Hemorrhoid Treatment

Active Ingredients

Lidocaine 4%
Phenylephrine HCL 0.25%

Purpose

Local Anesthetic
Vasoconstrictor

Uses

–Helps relieve the pain, itching, and burning associated with hemorrhoids.
–Temporarily reduce the swelling associated with irritated hemorrhoidal tissue and other anorectal disorders.
–Temporarily provides a coating for relief of anorectal discomforts.
–Temporarily protects irritated areas and inflamed perianal skin.

Warnings

For external use only.
Allergy Alert
Certain persons can develop allergic reactions to ingreadients in this product

Ask a doctor before use if you have:

–Heart disease; high blood pressure; thyroid disease; diabetes.
–Difficulty in urination due to enlargement of the prostate gland.

Ask a doctor or pharmacist before use if you are

presently taking a prescription drug for high blood pressure or depression.

When using this product

–Avoid contact with eyes.
–Do not exceed recommended daily dosage unless directed by a doctor.
–Do not put this product into the rectum by using fingers or any mechanical device or applicator.

Stop use and ask a doctor if

–Bleeding occurs.
–Condition worsens or does not improve within 7 days.
–Allergic reaction occurs to ingredients in this product.
–Symptom being treated does not subside or if redness, irritation, swelling, pain or other symptoms develop or increase.

If pregnant or breast-feeding,

ask a doctor before use.

Keep out of reach of children.

If swallowed, get medical help or contact a Poison Control Center right away.

Directions

–When practical, cleanse the affected area with mild soap and warm water and rinse thoroughly. Gently dry by patting or blotting with toilet tissue or soft cloth before applying.
–Adults and children 12 years and older: apply externally to the affected area up to 4 times daily.
–Children under 12 years of age: consult a doctor.

Other Information

–Store at 20-25°C (68-77°F). Excursions permitted to 10-30°C (59-86°F).

Inactive Ingredients

alcohol, aloe barbadensis leaf extract, beeswax, BHA, C12-15 alkyl benzoate, caprylic/capric triglyceride, caprylyl glycol, citric acid, cocos nucifera (coconut) oil, euphorbia cerifera (candelilla) wax, glycerin, glyceryl laurate, glyceryl undecylenate, hamamelis virginiana (witch hazel) water, helianthus annuus (sunflower) seed oil, lanolin, lanolin alcohol, lavandula angustifolia (lavender) flower oil, magnesium sulfate, petrolatum, tapioca starch, water (aqua).